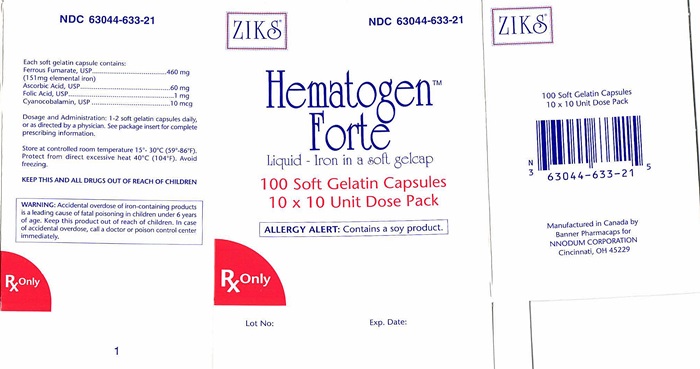 DRUG LABEL: HEMATOGEN FORTE
                
                
NDC: 63044-633 | Form: CAPSULE, GELATIN COATED
Manufacturer: Nnodum Pharmaceuticals
Category: prescription | Type: HUMAN PRESCRIPTION DRUG LABEL
Date: 20241228

ACTIVE INGREDIENTS: FERROUS FUMARATE 151 mg/1 1; ASCORBIC ACID 1 mg/1 1; FOLIC ACID 10 mg/1 1; CYANOCOBALAMIN 10 mg/1 1
INACTIVE INGREDIENTS: SOYBEAN OIL; LECITHIN, SOYBEAN; GLYCERIN; HYDROGENATED SOYBEAN OIL; TITANIUM DIOXIDE

Hematogen Forte

DESCRIPTION

Each brown soft gelatin capsule contains:

Ferrous fumarate............................................................................ 460 mg

(151 mg elemental iron)

Ascorbic acid.................................................................................... 60 mg

Folic acid............................................................................................ 1 mg

Cyanocobalamin.............................................................................10 mcg

The amount of elemental iron and the absorption of the iron components of commercial iron preparations vary widely. It is further established that certain "accessory components" may be included to enhance absorption and utilization of iron. Hematogen Forte Capsules are formulated to provide the essential factors for a complete, versatile hematinic.

Inactive Ingredients: Soybean oil, Lecithin, Glycerin, hydrogenated soybean oil, Yellow Beewax, Titanium Oxide.

ACTIONS/CLINICAL PHARMACOLOGY

High Elemental Iron Content: Ferrous fumarate, used in Hematogen Forte Capsules, is an organic iron complex which has the highest elemental iron content of any hematinic salt - 33%. This compares with 20% for 1,2 ferrous sulfate (heptahydrate) and 13% for ferrous gluconate. Hematogen Forte contains 151 mg of elemental iron.

More Complete Absorption: It has been repeatedly shown that ascorbic acid, when given in sufficient amounts, can increase the absorption of ferrous iron from the gastrointestinal tract. The absorption promoting effect is mainly due to the reducing action of ascorbic acid within the gastrointestinal lumen, 3 which help to prevent or delay the formation of insoluble or less dissociated ferric compounds.

Promotes Movement Of Plasma Iron: Ascorbic acid also plays an important role in the movement of plasma iron to storage depots in the tissues. The action, which leads to the transport of plasma iron to ferritin, presumably involves its reducing effect, converting transferrin iron from the ferric to the ferrous state. There is also evidence that ascorbic acid improves iron utilization, presumably as a further result of its reducing action, and some evidence that it may have a direct effect upon erythropoiesis. Ascorbic acid is further alleged to enhance the conversion of folic acid to a more physiologically active form, folinic acid, which would make it even more important in the treatment of anemia since it would aid in the utilization of dietary folic acid.

Excellent Oral Toleration: Ferrous fumarate is used in Hematogen Forte Capsules because it is less likely to cause the gastric disturbances so often associated with oral iron therapy. Ferrous fumarate has a low ionization constant and high solubility in the entire pH range of the gastrointestinal tract. It does not precipitate proteins or have the astringency of more ionizable forms of iron, and does not interfere with proteolytic or diastatic activities of the digestive system. Because of excellent oral toleration, Hematogen Forte Capsules can usually be administered between meals when iron absorption is maximal.

Folic Acid Supplementation: The use of supplemental folic acid may be indicated in patients with increased requirements for this vitamin, such as iron deficiency anemia. Folic acid administration may reduce the risk of neural tube defects in the developing fetus. Folic acid has also been shown to reduce circulating homocysteine levels in the blood. Folate as methyltetrahydrofolate and B as methylcobalamin are involved in the remethylation reaction of homocysteine to methionine. Elevated homocysteine plasma levels are associated with increased risk of preeclampsia, neural tube defects, myocardial infarction and atherosclerosis.

Toxicity: Ferrous fumarate was found to be the least toxic of three popular oral iron salts, with an oral LD 50 of 630 mg/kg. In the same report, the LD of ferrous gluconate was reported to be 320 mg/kg and ferrous sulfate 230 mg/kg.

INDICATIONS AND USAGE

For the treatment of all anemias responsive to oral iron therapy, such as hypochromic anemia associated with pregnancy, chronic or acute blood loss, dietary restriction, metabolic disease and post-surgical convalescence.

CONTRAINDICATIONS

Hemochromatosis and hemosiderosis are contraindications to iron therapy. Folic acid is contraindicated in patients with pernicious anemia (see PRECAUTIONS). Soybean oil, Lecithin, Di Calcium phosphate anhydrous, Beeswax yellow, hydrogenated soybean oil.

WARNING

WARNING: Accidental overdose of iron-containing products is a leading cause of fatal poisoning in children under 6. Keep this product out of reach of children. In case of accidental overdose, call a doctor or poison control center immediately.

ADVERSE REACTIONS

Average capsule doses in sensitive individuals or excessive dosage may cause nausea, skin rash, vomiting, diarrhea, precordial pain, or flushing of the face and extremities.

PRECAUTIONS

Folic acid should not be prescribed until the diagnosis of pernicious anemia has been eliminated, since it can alleviate the hematologic manifestations, while allowing neurological damage to 23 continue undetected

Pediatric Use

Safety and effectiveness in pediatric patients has not been established.

Geriatric Use

Clinical studies on this product have not been performed in sufficient numbers of subjects aged 65 and over to determine whether elderly subjects respond differently from younger subjects. In general, dose selection for an elderly patient should be cautious, usually starting at the low end of the dosage range, reflecting the greater frequency of decreased hepatic, renal, or cardiac function, and of noncomitant

DOSAGE AND ADMINISTRATION

Usual adult dose is 1-2 soft gelatin capsules daily, or as directed by a physician.

HOW SUPPLIED

Each brown soft gelatin capsule is imprinted with “ziks633” on one side. NDC 63044-0633-21, 10 x 10, Unit Dose Packs, In Packs of 100’s.

Store at controlled room temperature 15°- 30°C (59°- 86°F). Avoid excessive heat 40°C (104°F). Avoid freezing.

BIBILOGRAPHY

1Berk, M.S. and Novich, M.A.: “Treatment of Iron Deficiency Anemia With Ferrous Fumarate,“ Am. J. Obst. &2 3 Gynec., 203-206, 1962. Shapleigh, J.B., and Montgomery, A.:Am. Pract. & Dig. Treat. 10-461, 1959. Brise, H. and Hallberg, L.: “Effect of Ascorbic Acid on Iron Absorption,” Acta. Med. Scand.171:376, 51-58,19624 5 New Drugs, p. 309, AMA, Chicago, 1966. Mazur, A., Green, S. and Carleton, A,: “Mechanism of Plasma 6 Iron Incorporation into Hepatic Ferritin”J. Bio. Chem. 3:595-603, 1960. Greenberg, S.M. Tucker, A. E., Mathues, H and J.D.: “Iron Absorption and Metabolism, I. Interrelationship of Ascorbic Acid and Vitamin E,” 7 J. Nutrition 63:19-31, 1957. Moore, C.V. and Dubach, R. “Observations on the Absorption of Iron from 8 Foods Tagged with Radioiron" Trans. Assoc. Amer. Physic. 64:245, 1951. Steinkamp, R. Dubach, R. and 9 Moore, C.V.: “Studies in Iron Transportation and Metabolism,” Arch. Int. Med. 95:181,1955. Gorten, M. K. and Bradley, J. E.: “The Treatment of Nutritional Anemia in Infancy and Childhood with Oral Iron and Ascorbic Acid,"J. Pediatrics, 45:1,1954. '°Mazur, A.: "Role of Ascorbic Acid in the Incorporation of Plasma 11 Iron into Ferritin," Ann. N.Y. Acad. Sci, 92:223-229, 1961. Cox, E.V. et al.: “The Anemia of Scurvy,” Amer. J. 12 Med. 42:220-227, 1967. McEvoy, G.K., Ed.: AHFS Drug Information, p. 2667-2669, Am. Soc. Hosp.13 Pharm., Bethesda, 1996. Franken DG, Boers GH, Blom HJ, Trijbels JM. "Effect of various regimens of vitamin B and folic acid on mild hyperhomocysteinemia in vascular patients." J. Inherit. Metab. Dis. 1994; 6 14 17:159-62. Brattstrom L, Israelsson B, Norrving B, et al. "Impaired homocysteine metabolism in earlyonset cerebral and peripheral occlusive disease - effects of pyridoxine and folic acid treatment.” 15 Atherosclerosis 1990; 81: 2004-6. Kang S. Wong PWK, Norusis M. “Homocysteinemia due to folate 16 deficiency.” Metabolism 1987; 36: 458-62. Alien RH, Stabler SP, Savage DG, Lindernbaum J. "Diagnosis of cobalamin deficiency.” 17 Am. J. Hematol. 1990; 34: 90-98. Dekker GA, de Vries Jl, Doelitzsch PM, Huijgens PC, von Blomberg BM, Jakobs, C, van Geijn HP. 1985. "Underlying disorder associated with severe early-onset preeclampsia.” Am. J. 18 Obstet. Gynecol. 173:1042-1048. Mills JL, McPartlin JM, Kirke PN, Lee YJ, Conley MR, Weir DG, Scott JM. 1995. “Homocysteine metabolism in pregnancies complicated by neural-tube defects.” Lancet. 345: 149- 19 151. Steegers-Theunissen RP, Boers GH, Blom HJ, Nijhuis JG, Thomas CM, Borm GF, Eskes TK. 1995. "Neural tube defects and elevated homocysteine levels in amniotic fluid.” Am. J. Obstet. Gynecol. 172:1436-1441. 20Landgren F, Israelsson B, Lindgren A, Hultberg B, Andersson A, Brattstrom L. 1995. “Plasma homocysteine in 21 acute myocardial infarction: Homocysteine-lowering effect of folic acid.” J. Intern. Med. 237: 381-388. Mayor EL, Jacobsen DW, Robinson K. 1996. "Homocysteine and Coronary Atherosclerosis." J. Am. Coll. Cardiol. 22 23 27:517-27. Berenbaum, M.C. et al.: Blood, 15:540,1960. Drug Information for the Health Care Professional, p.1365-1368, U. S. Pharmacopeial Conven., Rockville, 1995.

Manufactured by:

Catalent Australia PTY LTD

Distributed by:

Nnodum Pharmaceuticals

Cincinnati, Ohio 45229